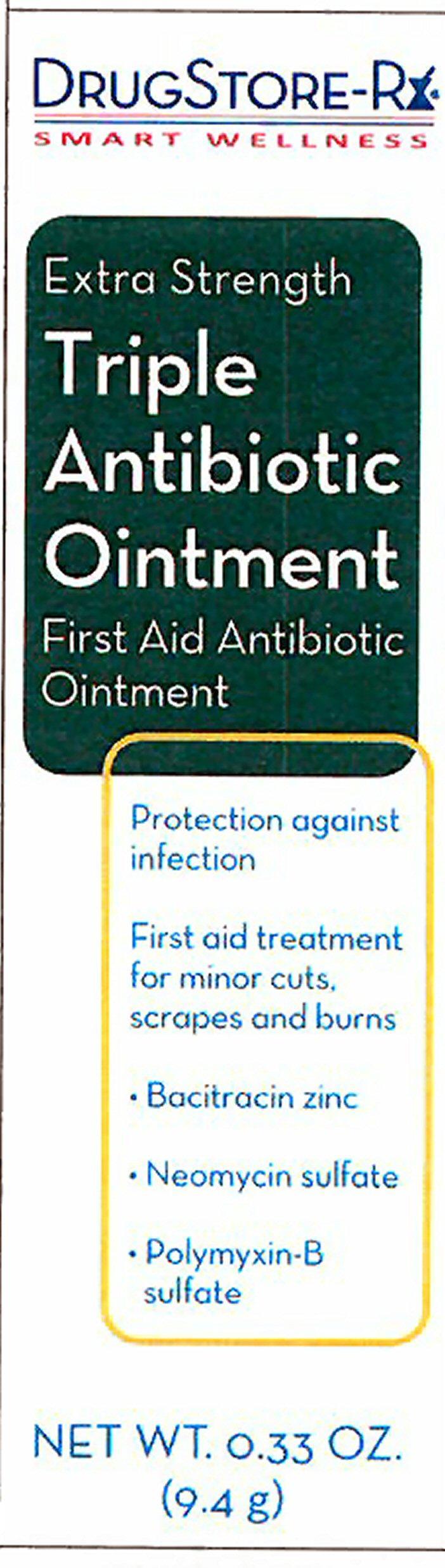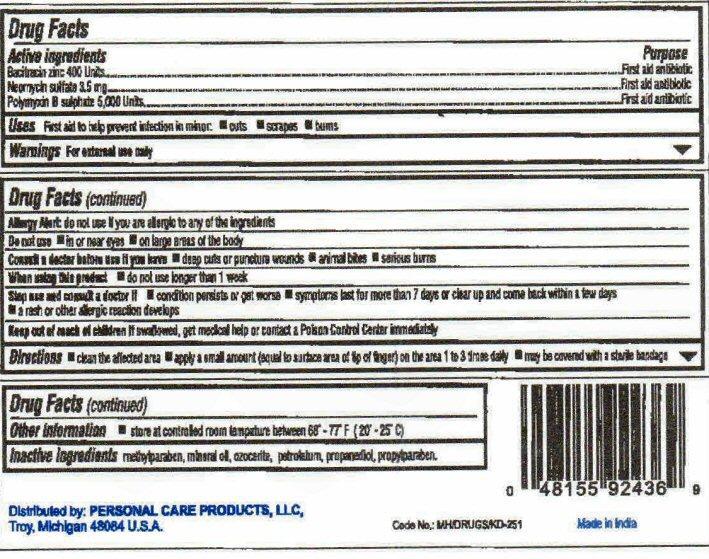 DRUG LABEL: Triple Antibiotic
NDC: 29500-2436 | Form: OINTMENT
Manufacturer: Personal Care Products, Inc.
Category: otc | Type: HUMAN OTC DRUG LABEL
Date: 20130711

ACTIVE INGREDIENTS: BACITRACIN ZINC 400 [iU]/9.4 g; NEOMYCIN SULFATE 3.5 mg/9.4 g; POLYMYXIN B SULFATE 5000 [iU]/9.4 g
INACTIVE INGREDIENTS: METHYLPARABEN; MINERAL OIL; CERESIN; PETROLATUM; PROPANEDIOL; PROPYLPARABEN

Active ingredients

Drug Facts

Bacitracin zinc 400 Units

Neomycin sulfate 3.5 mg

Polymyxin B sulfate 5,000 Units

Purpose

First aid antibiotic

Keep out of reach of children. If swallowed, get medical help or contact a Poison Control Center immediately.

Uses

First aid to help prevent infection in minor

- cuts
- scrapes
- burns

Warnings

For external use only

Allergy Alert: do not use if you are allergic to any of the ingredients

Do not use

- in or near eyes
- on large areas of the body
- Consult a doctor before use if you have

Directions

- clean the affected area
- apply a small amount (equal to surface area of tip of finger) on the area 1 to 3 times daily
- may be covered with a sterile bandage

Other information

- store at controlled room temperature between 68° - 77° F (20° - 25° C)

Inactive ingredients

methylparaben, mineral oil, ozocerite, petrolatum, propanediol, propylparaben

Product Label

DRUGSTORE-Rx
SMART WELLNESS
Extra Strength

Triple Antibiotic Ointment
First Aid Antibiotic Ointment

Protection against infection

First aid treatment for minor cuts, scrapes and burns

- Bacitracin zinc
- Neomycin sulfate
- Polymyxin-B sulfate

NET WT. 0.33 OZ. (9.4 g)
Distributed by: PERSONAL CARE PRODUCTS, LLC
Troy, Michigan 48084 U.S.A.
Code No. MH/DRUGS/KD-313 Made in India